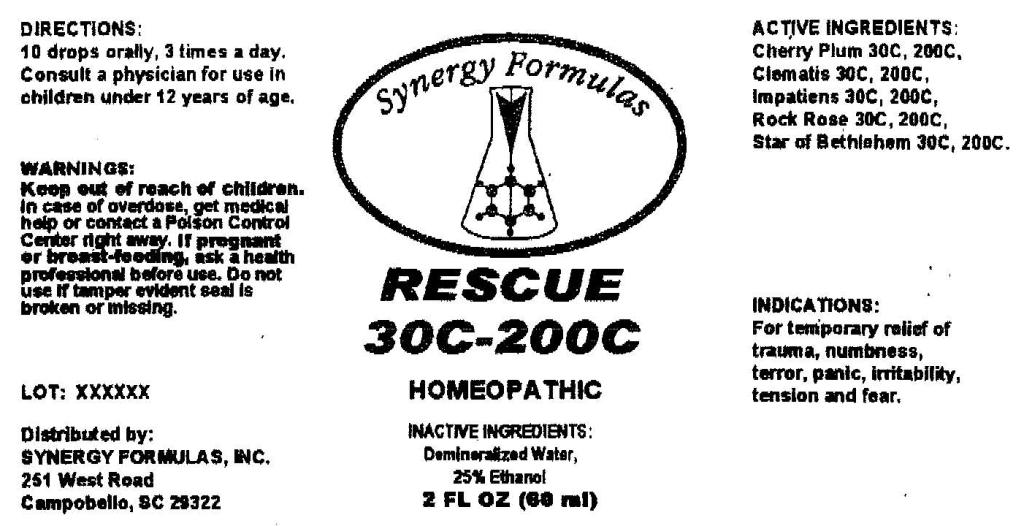 DRUG LABEL: Rescue
NDC: 57520-0570 | Form: LIQUID
Manufacturer: Apotheca Company
Category: homeopathic | Type: HUMAN OTC DRUG LABEL
Date: 20110103

ACTIVE INGREDIENTS: PRUNUS CERASIFERA FLOWER 200 [hp_M]/1 mL; CLEMATIS VITALBA FLOWER 200 [hp_C]/1 mL; IMPATIENS GLANDULIFERA FLOWER 200 [hp_C]/1 mL; HELIANTHEMUM NUMMULARIUM FLOWER 200 [hp_C]/1 mL; ORNITHOGALUM UMBELLATUM 200 [hp_C]/1 mL
INACTIVE INGREDIENTS: WATER; ALCOHOL

Rescue 30C 200C

ACTIVE INGREDIENT

ACTIVE INGREDIENTS: Cherry plum 30C, 200C, Clematis 30C, 200C, Impatiens 30C, 200C, Rock Rose 30C, 200C, Star of bethlehem 30C, 200C.

PURPOSE

INDICATIONS: For temporary relief of trauma, numbness, terror, panic, irritability, tension and fear.

WARNINGS

WARNINGS: Keep out of reach of children. In case of overdose, get medical help or contact a Poison Control Center right away.

If pregnant or breast-feeding, ask a health professional before use.

Do not use if tamper evident seal is broken or missing.

DOSAGE AND ADMINISTRATION

DIRECTIONS: 10 drops orally, 3 times a day. Consult a physician for use in children under 12 years of age.

INACTIVE INGREDIENTS: Demineralized water, 25% Ethanol.

KEEP OUT OF REACH OF CHILDREN. In case of overdose, get medical help or contact a Poison Control Center right away.

INDICATIONS AND USAGE

INDICATIONS: For temporary relief of trauma, numbness, terror, panic, irritability, tension and fear.

QUESTIONS

Distributed by:

SYNERGY FORMULAS, INC.

251 West Road

Campobello, SC 29322

PACKAGE LABEL

Synergy Formulas

RESCUE 30C 200C

HOMEOPATHIC

2 FL OZ (60 ml)